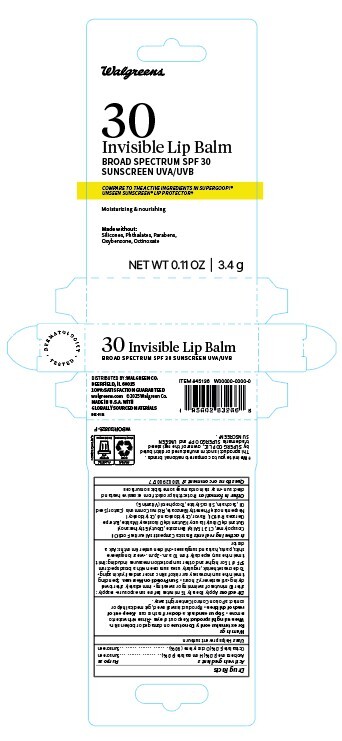 DRUG LABEL: Walgreens Invisible Lip Balm
NDC: 0363-9785 | Form: STICK
Manufacturer: Walgreens
Category: otc | Type: HUMAN OTC DRUG LABEL
Date: 20251124

ACTIVE INGREDIENTS: AVOBENZONE 30 mg/1 g; HOMOSALATE 90 mg/1 g; OCTISALATE 50 mg/1 g; OCTOCRYLENE 90 mg/1 g
INACTIVE INGREDIENTS: OCTYLDODECANOL 415 meq/1 g; CASTOR OIL 40 mg/1 g

Drug Facts

Active ingredient

Avobenzone 3.0%, Homosalate 9.0%, Octisalate 5.0%, Octocrylene 9.0%

Purpose

Sunscreen

Keep Out of Reach of Children

If product is swallowed, get medical help or contact a Poison Control Center right away.

Uses

Helps prevent sunburn.

Warnings

For external use only. Do not use on damaged or broken skin. When using this product: Keep out of eyes. Risnse with water to remove. Stop use and ask a doctor if ·rash occurs·

Directions

Apply liberally 15 minutes before sun exposure. Reapply; after 80 minutes of swimming or sweating. Immediately after towel drying.at least every 2 hours. Sun Protection Measures: Spending time in the sun increases your risk of skin cancer and early skin aging. To decrease the risk, regularly use a sunscreen with a broad spectrum SPF of 15 or higher and other sun protection measures including: limit time in the sun, especially from 10 a.m. – 2 p.m. wear long sleeve shirts, pants, hats, and sunglasses. Children under 6 months: Ask a doctor.

Inactive Ingredients

Brassica Campestris/Aleurites Fordi Oil Crosspolymer, C12-15 Alkyl Benzoate, Dibutyl Ethylhexanoyl Glutamide, Dibutyl Lauroyl Glutamide, Diisostearyl Malate, Euterpe Oleracea Fruit Oil, Flavor, Octyldodecanol, Octyldodecyl Neopentanoate, Phenethyl Benzoate, Ricinus Communis (Castor) Seed Oil, Saccharin, Silica Silylate, Tocopherol (Vitamin E)

Questions

1-800-290-0577